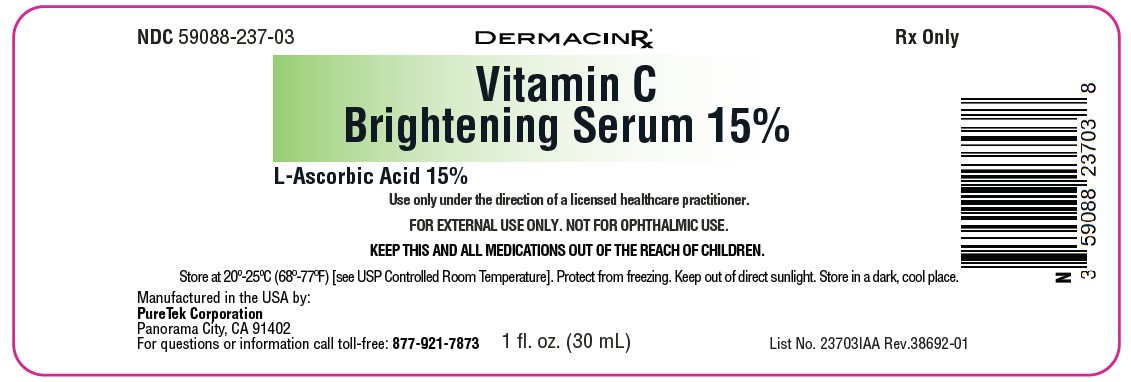 DRUG LABEL: Vitamin C 15 %
NDC: 59088-237 | Form: LIQUID
Manufacturer: PURETEK CORPORATION
Category: prescription | Type: HUMAN PRESCRIPTION DRUG LABEL
Date: 20240506

ACTIVE INGREDIENTS: ASCORBIC ACID 15 mg/100 mL
INACTIVE INGREDIENTS: SAFFLOWER OIL; BUTYLENE GLYCOL; LAVENDER OIL; PANTHENOL; ROSA DAMASCENA FLOWER OIL; DIETHYLENE GLYCOL MONOETHYL ETHER; POLYOXYL 40 HYDROGENATED CASTOR OIL; VETIVER OIL; YLANG-YLANG OIL; .ALPHA.-TOCOPHEROL, D-; LAURETH-23; ADZUKI BEAN; PROPYLENE GLYCOL; FERULIC ACID; PHENOXYETHANOL; WATER; ETHYLHEXYLGLYCERIN; GLYCERIN

Vitamin C 15
Rx Only

FOR EXTERNAL USE ONLY. NOT FOR OPHTHALMIC USE.

Vitamin C Brightening Serum 15%

Active Ingredient: L-ascorbic acid 15%

Inactive Ingredients:
Aqua (Purified Water), Bacillus/Cordyceps Sinensis/Ganoderma Lucidum/Inonotus Obliquus/Lentinus Edodes/Phellinus Linteus/Schizophyllum Commune/Tricholoma Matsutake Extract Ferment Filtrate, Butylene Glycol, Cananga Odorata (Ylang Ylang) Flower Oil, GenRx Complex® (proprietary blend), D-alpha Tocopherol, Ethoxydiglycol, Ethylhexylglycerin, Ferulic Acid, Fragrance, Glycerin, Lactobacillus Ferment, Lactobacillus/Centella Asiatica/Gleditsia Sinensis Thorn/Houttuynia Cordata Extract/Phellodendron Amurense Bark/Polygonum Cuspidatum Root/Prunella Vulgaris/Torilis Japonica Extract Ferment Filtrate, Lactobacillus/Rice Ferment Filtrate, Laureth-23, Lavandula Angustifolia (Lavender) Oil, Panthenol, PEG-40 Hydrogenated Castor Oil, Phaseolus Angularis Seed Extract, Phenoxyethanol, Propylene Glycol, Rosa Damascena (Rose) Flower Oil, Saccharomyces/Camellia Sinensis Extract Ferment Filtrate, Vetiveria Zizanoides (Vetiver) Root Oil.

DESCRIPTION

This potent daily antioxidant serum contains 15% L-ascorbic acid, along with a GenRx Complex® to further enhance the serum's effects. It helps protect against free radicals throughout the day, brightens skin tone, and lessens signs of previous skin damage.

Key Benefits:

• A potent antioxidant that strengthens the skin's natural defenses, brightening the skin and minimizing the effects of previous visible damage.
• Improves the look of wrinkles and fine lines, benefiting the skin.
• Strengthens the skin's defense mechanisms against free radicals and environmental stressors.
• Essential for collagen biosynthesis and has the antiaging effect

Safety Information:

• Only for external use.
• Avoid making direct contact with your lips, mouth, nose, or eyes.
• A very small number of users of this product might experience a slight tingling; this should go away with continued use.
• If tingling gets worse, stop using and get medical attention.

Direction:

Step 1: Cleanse the face, then apply 4-5 drops of serum in the morning after cleansing and toning.
Step 2: Wait for the serum to be absorbed into the skin.
Step 3: Apply moisturizer and SPF.

How Supplied:

Vitamin C Brightening Serum 15% is provided in a 1 fl. oz. (30 mL) bottle with NDC 59088-237-03

Storage:

Keep out of direct sunlight.
KEEP THIS AND ALL MEDICATIONS OUT OF THE REACH OF CHILDREN.
Store at 20° to 25°C (68° to 77°F) [see USP Controlled Room Temperature]. Protect from freezing. Keep out of direct sunlight. Store in a dark, cool place.

This product may undergo a gradual color change to a brown hue as it ages. This change is a natural occurrence and does not affect the product's quality, safety, or effectiveness. The product remains safe for use within its specified shelf life.

Keep cap on tightly.

Vitamin C Brightening Serum 15%

Manufactured in the USA by:
PureTek Corporation
Panorama City, CA 91402
For questions or information
call toll-free: 877-921-7873